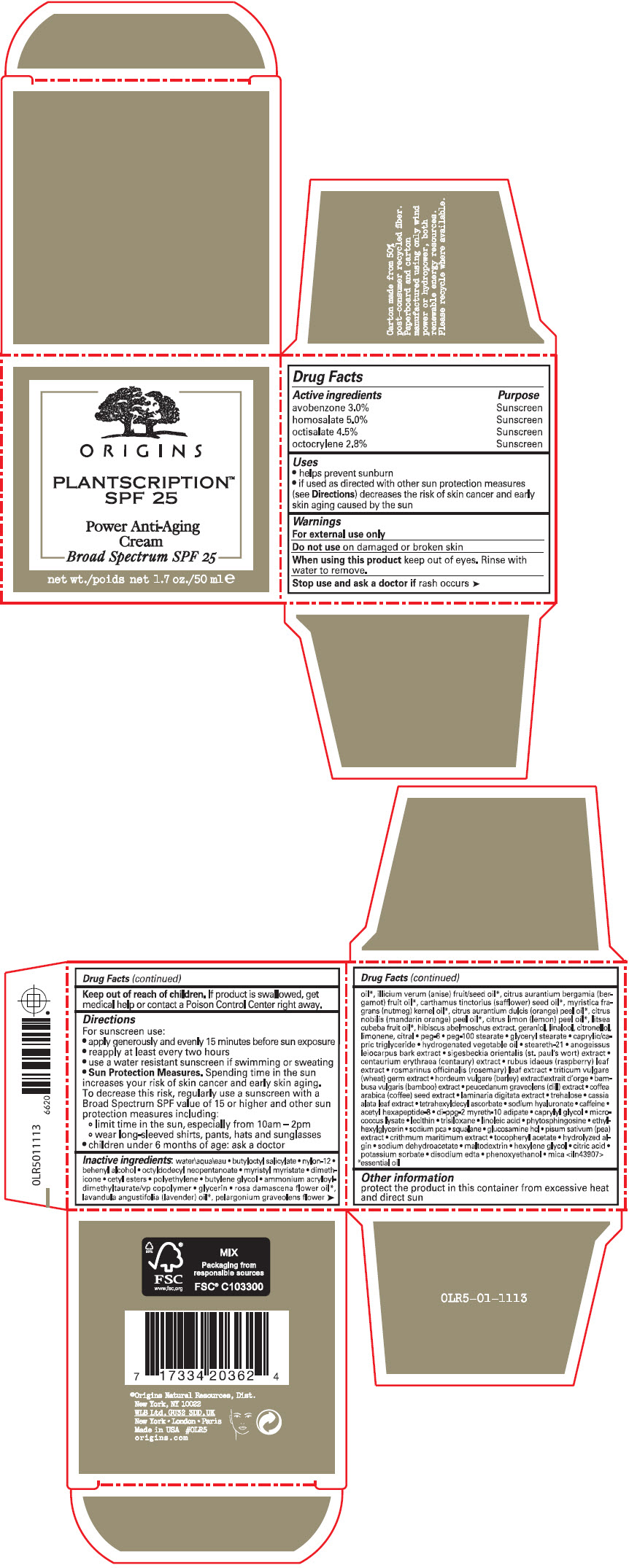 DRUG LABEL: PLANTSCRIPTION SPF 25 POWER ANTI AGING BROAD SPECTRUM 25
NDC: 59427-114 | Form: CREAM
Manufacturer: ORIGINS NATURAL RESOURCES INC.
Category: otc | Type: HUMAN OTC DRUG LABEL
Date: 20230911

ACTIVE INGREDIENTS: AVOBENZONE 30 mg/1 mL; HOMOSALATE 50 mg/1 mL; OCTISALATE 45 mg/1 mL; OCTOCRYLENE 28 mg/1 mL
INACTIVE INGREDIENTS: WATER; BUTYLOCTYL SALICYLATE; NYLON-12; DOCOSANOL; OCTYLDODECYL NEOPENTANOATE; MYRISTYL MYRISTATE; DIMETHICONE; CETYL ESTERS WAX; HIGH DENSITY POLYETHYLENE; BUTYLENE GLYCOL; AMMONIUM ACRYLOYLDIMETHYLTAURATE/VP COPOLYMER; GLYCERIN; ROSA X DAMASCENA FLOWER OIL; LAVENDER OIL; PELARGONIUM GRAVEOLENS FLOWER OIL; ANISE; BERGAMOT OIL; SAFFLOWER OIL; NUTMEG OIL; ORANGE OIL, COLD PRESSED; MANDARIN OIL; LEMON OIL, COLD PRESSED; LITSEA OIL; GERANIOL; LINALOOL, (+/-)-; .BETA.-CITRONELLOL, (R)-; CITRAL; POLYETHYLENE GLYCOL 300; PEG-100 STEARATE; GLYCERYL MONOSTEARATE; MEDIUM-CHAIN TRIGLYCERIDES; STEARETH-21; CENTAURIUM ERYTHRAEA; RASPBERRY; ROSEMARY; WHEAT; BARLEY; DILL; TREHALOSE; TETRAHEXYLDECYL ASCORBATE; HYALURONATE SODIUM; CAFFEINE; ACETYL HEXAPEPTIDE-8; DI-PPG-2 MYRETH-10 ADIPATE; CAPRYLYL GLYCOL; TRISILOXANE; LINOLEIC ACID; PHYTOSPHINGOSINE; ETHYLHEXYLGLYCERIN; SODIUM PYRROLIDONE CARBOXYLATE; SQUALANE; GLUCOSAMINE HYDROCHLORIDE; PEA; SODIUM DEHYDROACETATE; MALTODEXTRIN; HEXYLENE GLYCOL; CITRIC ACID MONOHYDRATE; POTASSIUM SORBATE; EDETATE DISODIUM ANHYDROUS; PHENOXYETHANOL; MICA

PLANTSCRIPTION™ SPF 25 POWER ANTI AGING CREAM BROAD SPECTRUM 25

Drug Facts

ACTIVE INGREDIENT

Active ingredients | Purpose
avobenzone 3.0% | Sunscreen
homosalate 5.0% | Sunscreen
octisalate 4.5% | Sunscreen
octocrylene 2.8% | Sunscreen

Uses

- helps prevent sunburn
- if used as directed with other sun protection measures (see Directions) decreases the risk of skin cancer and early skin aging caused by the sun

Warnings

For external use only

Do not use on damaged or broken skin

When using this product keep out of eyes. Rinse with water to remove.

Stop use and ask a doctor if rash occurs

Keep out of reach of children. If product is swallowed, get medical help or contact a Poison Control Center right away.

Directions

For sunscreen use:

- apply generously and evenly 15 minutes before sun exposure
- reapply at least every two hours
- use a water resistant sunscreen if swimming or sweating
- Sun Protection Measures. Spending time in the sun increases your risk of skin cancer and early skin aging. To decrease this risk, regularly use a sunscreen with a Broad Spectrum SPF value of 15 or higher and other sun protection measures including:
  - limit time in the sun, especially from 10am – 2pm
  - wear long-sleeved shirts, pants, hats and sunglasses
- children under 6 months of age: ask a doctor

Inactive ingredients

water\aqua\eau • butyloctyl salicylate • nylon-12 • behenyl alcohol • octyldodecyl neopentanoate • myristyl myristate • dimethicone • cetyl esters • polyethylene • butylene glycol • ammonium acryloyldimethyltaurate/vp copolymer • glycerin • rosa damascena flower oil [essential oil] , lavandula angustifolia (lavender) oil , pelargonium graveolens flower oil , illicium verum (anise) fruit/seed oil , citrus aurantium bergamia (bergamot) fruit oil , carthamus tinctorius (safflower) seed oil , myristica fragrans (nutmeg) kernel oil , citrus aurantium dulcis (orange) peel oil , citrus nobilis (mandarin orange) peel oil , citrus limon (lemon) peel oil , litsea cubeba fruit oil , hibiscus abelmoschus extract, geraniol, linalool, citronellol, limonene, citral • peg-6 • peg-100 stearate • glyceryl stearate • caprylic/capric triglyceride • hydrogenated vegetable oil • steareth-21 • anogeissus leiocarpus bark extract • sigesbeckia orientalis (st. paul's wort) extract • centaurium erythraea (centaury) extract • rubus idaeus (raspberry) leaf extract • rosmarinus officinalis (rosemary) leaf extract • triticum vulgare (wheat) germ extract • hordeum vulgare (barley) extract\extrait d'orge • bambusa vulgaris (bamboo) extract • peucedanum graveolens (dill) extract • coffea arabica (coffee) seed extract • laminaria digitata extract • trehalose • cassia alata leaf extract • tetrahexyldecyl ascorbate • sodium hyaluronate • caffeine • acetyl hexapeptide-8 • di-ppg-2 myreth-10 adipate • caprylyl glycol • micrococcus lysate • lecithin • trisiloxane • linoleic acid • phytosphingosine • ethylhexylglycerin • sodium pca • squalane • glucosamine hcl • pisum sativum (pea) extract • crithmum maritimum extract • tocopheryl acetate • hydrolyzed algin • sodium dehydroacetate • maltodextrin • hexylene glycol • citric acid • potassium sorbate • disodium edta • phenoxyethanol • mica <iln43907>

Other information

protect the product in this container from excessive heat and direct sun

PRINCIPAL DISPLAY PANEL - 50 ml Jar Carton

ORIGINS

PLANTSCRIPTION™
SPF 25

Power Anti-Aging
Cream
Broad Spectrum SPF 25

net wt. 1.7 oz./50 ml e